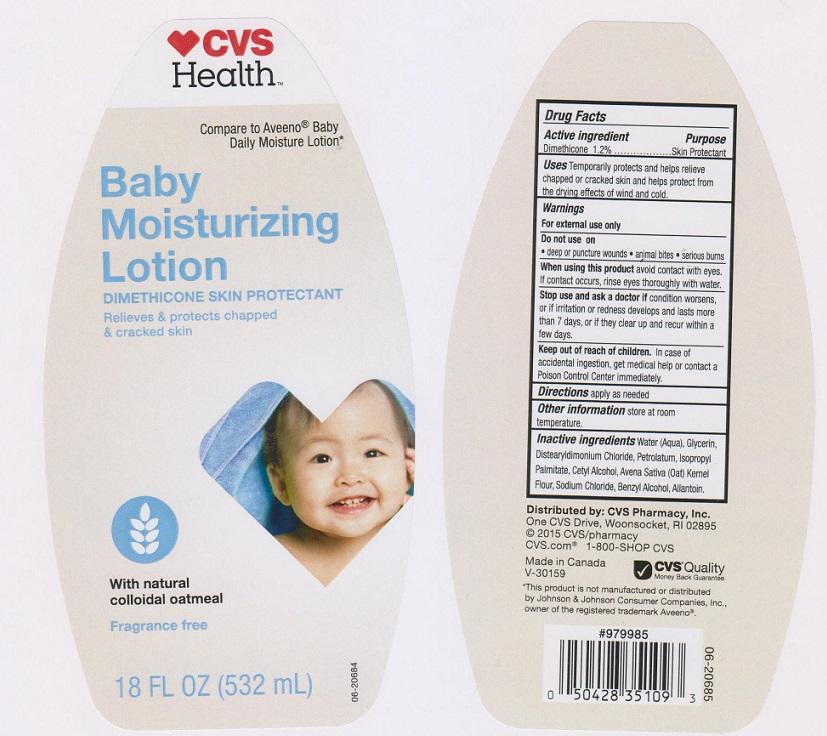 DRUG LABEL: CVS PHARMACY
NDC: 59779-358 | Form: LIQUID
Manufacturer: CVS PHARMACY
Category: otc | Type: HUMAN OTC DRUG LABEL
Date: 20151119

ACTIVE INGREDIENTS: DIMETHICONE 12 mg/1 mL
INACTIVE INGREDIENTS: WATER; GLYCERIN; DISTEARYLDIMONIUM CHLORIDE; PETROLATUM; ISOPROPYL PALMITATE; CETYL ALCOHOL; OATMEAL; SODIUM CHLORIDE; BENZYL ALCOHOL; ALLANTOIN

DRUG FACTS

Active ingredient

Dimethicone 1.2%

Purpose

Skin Protectant

Uses

Temporarily protects and helps relieve chapped or cracked skin and helps protect from the drying effects of wind and cold.

Warnings

For external use only

Do not use on

- deep or puncture wounds
- animal bites
- serious burns

When using this product

avoid contact with eyes. If contact occurs, rinse eyes thoroughly with water.

Stop use and ask a doctor if

condition worsens, or if irritation or redness develops and lasts more than 7 days, or if they clear up and recur within a few days.

Keep out of reach of children.

In case of accidental ingestion, get medical help or contact a Poison Control Center immediately

Directions

apply as needed

Other information

Store at room temperature

Inactive ingredients

Water (Aqua), Glycerin, Distearyldimonium Chloride, Petrolatum, Isopropyl Palmitate, Cetyl Alcohol, Avena Sativa (Oat) Kernel Flour, Sodium Chloride, Benzyl Alcohol, Allantoin.